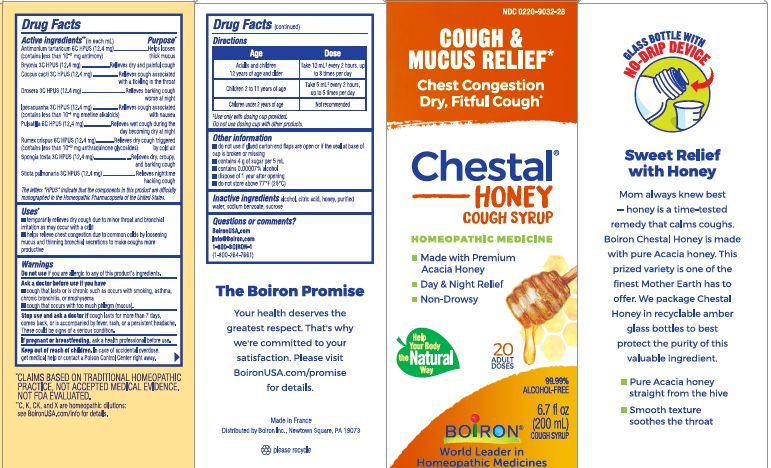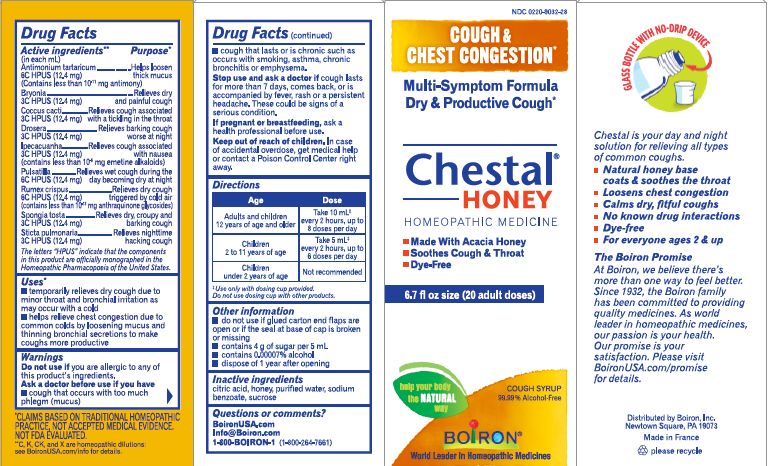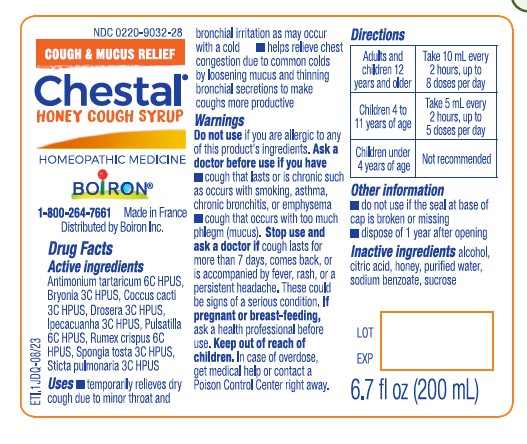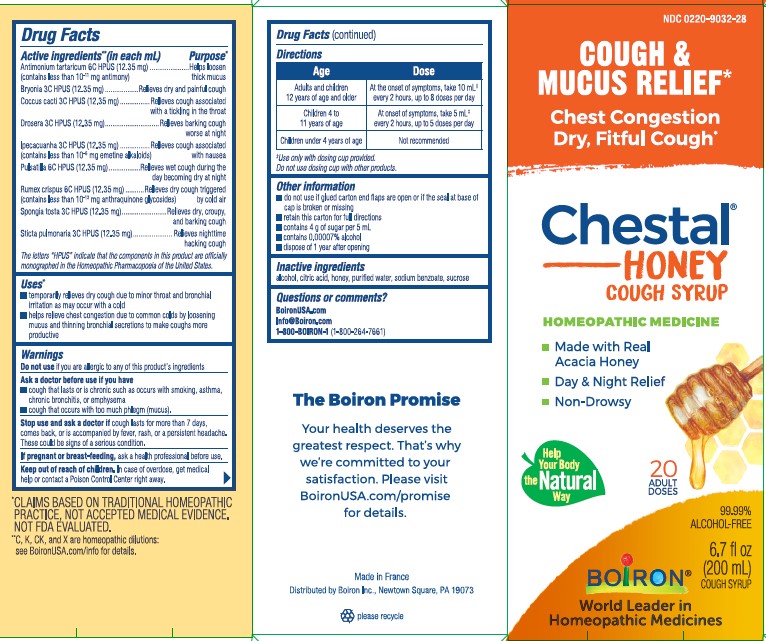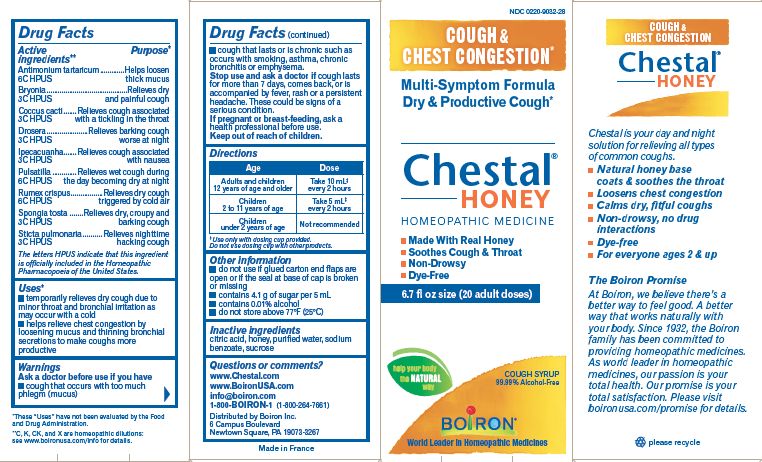 DRUG LABEL: Chestal
NDC: 0220-9032 | Form: SYRUP
Manufacturer: Laboratoires Boiron
Category: homeopathic | Type: HUMAN OTC DRUG LABEL
Date: 20230911

ACTIVE INGREDIENTS: BRYONIA ALBA ROOT 3 [hp_C]/1 mL; PROTORTONIA CACTI 3 [hp_C]/1 mL; DROSERA ROTUNDIFOLIA FLOWERING TOP 3 [hp_C]/1 mL; IPECAC 3 [hp_C]/1 mL; PULSATILLA VULGARIS 6 [hp_C]/1 mL; RUMEX CRISPUS ROOT 6 [hp_C]/1 mL; SPONGIA OFFICINALIS SKELETON, ROASTED 3 [hp_C]/1 mL; LOBARIA PULMONARIA 3 [hp_C]/1 mL; ANTIMONY POTASSIUM TARTRATE 6 [hp_C]/1 mL
INACTIVE INGREDIENTS: HONEY; SUCROSE; WATER; CITRIC ACID MONOHYDRATE; SODIUM BENZOATE; ALCOHOL

Chestal Adult Honey

Active ingredients** (in each mL)

Antimonium tartaricum 6C HPUS (12.35 mg) (contains less than 10^-11 mg antimony)

Bryonia 3C HPUS (12.35 mg)

Coccus cacti 3C HPUS (12.35 mg)

Drosera 3C HPUS (12.35 mg)

Ipecacuanha 3C HPUS (12.35 mg) (contains less than 10-6 mg emetine alkaloids)

Pulsatilla 6C HPUS (12.35 mg)

Rumex crispus 6C HPUS (12.35 mg) (contains less than 10^-13 mg anthraquinone glycosides)

Spongia tosta 3C HPUS (12.35 mg)

Sticta pulmonaria 3C HPUS (12.35 mg)

The letters "HPUS" indicate that the components in this product are officially monographed in the Homeopathic Pharmacopoeia of the United States.

Purpose*

Antimonium tartaricum 6C HPUS ... Helps loosen thick mucus
Bryonia 3C HPUS ... Relieves dry and painful cough
Coccus cacti 3C HPUS ... Relieves cough associated with a tickling in the throat
Drosera 3C HPUS ... Relieves barking cough worse at night
Ipecacuanha 3C HPUS ... Relieves cough associated with nausea
Pulsatilla 6C HPUS ... Relieves wet cough during the day becoming dry at night
Rumex crispus 6C HPUS ... Relieves dry cough triggered by cold air
Spongia tosta 3C HPUS ... Relieves dry, croupy and barking cough
Sticta pulmonaria 3C HPUS ... Relieves nighttime hacking cough

Uses*

temporarily relieves dry cough due to minor throat and bronchial irritation as may occur with cold

helps relieve chest congestion due to common colds by loosening mucus and thinning bronchial secretions to make coughs more productive

Do not use if you are allergic to any of this product's ingredients.

Ask a doctor before use if you have

cough that lasts or is chronic such as occurs with smoking, asthma, chronic bronchitis or emphysema

cough that occurs with too much phlegm (mucus).

Stop use and ask a doctor if cough lasts for more than 7 days, comes back, or is accompanied by fever, rash, or a persistent headache. These could be a sign of a serious condition.

PREGNANCY OR BREAST FEEDING

If pregnant or breast-feeding, ask a health professional before use.

Keep out of reach of children. In case of accidental overdose, get medical help or contact a Poison Control Center right away.

DOSAGE AND ADMINISTRATION

Adults and children 12 years of age and older - At the onset of symptoms, take 10 mL + every 2 hours, up to 8 doses per day

Children 4 to 11 years of age - At the onset of symptoms, take 5 mL+ every 2 hours, up to 5 doses per day

Children under 4 years of age - Not recommended

^+ Use only with dosing cup provided

Do not use dosing cup with other products.

INACTIVE INGREDIENT

alcohol, citric acid, honey, purified water, sodium benzoate, sucrose

Questions, Comments
Boironusa.com
info@boironusa.com
1-800-BOIRON-1 (1-800-264-7661)
Distributed by Boiron, Inc.
Newtown Square, PA 19073-3267

Made in France

do not use if glued carton end flaps are open or if the seal at base of cap is broken or missing

retain this carton for full directions

contains 4 g of sugar per 5 mL

contains 0.00007% alcohol

dispose of 1 year after opening

6.7 fl oz (200 mL) cough syrup

20 Adult Doses

Multi-Symptom Cough & Mucus Relief*

Cough & Mucus Relief*

Chest Congestion, Dry, Fitful Cough*

Made with Real Acacia Honey

Day & Night Relief

Non-Drowsy

*CLAIMS BASED ON TRADITIONAL HOMEOPATHIC PRACTICE NOT ACCEPTED MEDICAL EVIDENCE. NOT FDA EVALUATED.

**C,K,CK, and X are homeopathic dilutions: see BoironUSA.com/info for details.